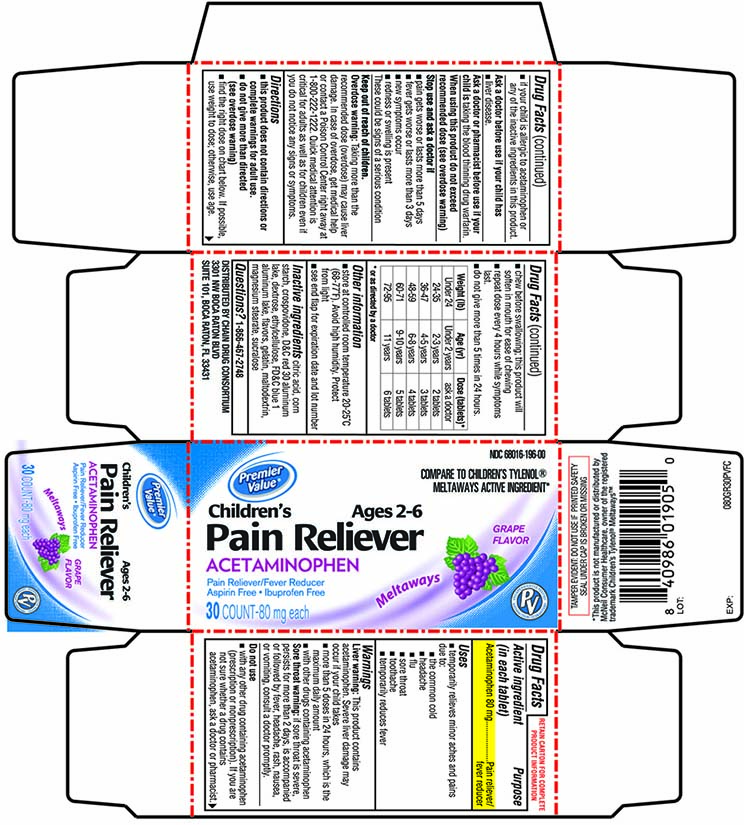 DRUG LABEL: Premier Value Childrens Acetaminophen Melts
NDC: 68016-196 | Form: TABLET, CHEWABLE
Manufacturer: Chain Drug Consortium
Category: otc | Type: HUMAN OTC DRUG LABEL
Date: 20150116

ACTIVE INGREDIENTS: ACETAMINOPHEN 80 mg/1 1
INACTIVE INGREDIENTS: CITRIC ACID MONOHYDRATE; STARCH, CORN; CROSPOVIDONE (15 MPA.S AT 5%); D&C RED NO. 30; DEXTROSE, UNSPECIFIED FORM; ETHYLCELLULOSES; FD&C BLUE NO. 1; GELATIN; MALTODEXTRIN; MAGNESIUM STEARATE; SUCRALOSE

Premier Value Children’s Pain Reliever

Active ingredient (in each tablet)

Acetaminophen 80 mg

Purpose

Pain reliever/fever reducer

Uses

- temporarily relieves minor aches and pains due to:
  - the common cold
  - headache
  - flu
  - sore throat
  - toothache
- temporarily reduces fever

Warnings

Liver warning: This product contains acetaminophen. Severe liver damage may occur if your child takes:

- more than 5 doses in 24 hours, which is the maximum daily amount
- with other drugs containing acetaminophen

Sore throat warning: If sore throat is severe, persists for more than 2 days, is accompanied or followed by fever, headache, rash, nausea, or vomiting, consult a doctor promptly.

Do not use

- with any other drug containing acetaminophen (prescription or nonprescription). If you are not sure whether a drug contains acetaminophen, ask a doctor or pharmacist.
- if your child is allergic to acetaminophen or any of the inactive ingredients in this product

Ask a doctor before use if your child has

liver disease.

Ask a doctor or pharmacist before use if your child is

taking the blood thinning drug warfarin.

When using this product

do not exceed recommended dosage.

Stop use and ask a doctor if

- pain gets worse or lasts more than 5 days
- fever gets worse or lasts more than 3 days
- new symptoms occur
- redness or swelling is present

These could be signs of a serious condition.

Keep out of reach of children.

Overdose warning: Taking more than the recommended dose (overdose) may cause liver damage. In case of overdose, get medical help or contact a Poison Control Center right away at 1-800-222-1222. Quick medical attention is critical for adults as well as for children even if you do not notice any signs or symptoms.

Directions

- this product does not contain directions or complete warnings for adult use
- do not give more than directed (see overdose warning)
- find the right dose on chart. If possible, use weight to dose; otherwise, use age.
- Chew before swallowing; this product will soften in mouth for ease of chewing
- repeat dose every 4 hours while symptoms last
- do not give more than 5 times in 24 hours
- do not give for more than 5 days unless directed by a doctor

Weight (lb) | Age (yr) | Dose (tablets)*
Under 24 | Under 2 years | ask a doctor
24-35 | 2-3 years | 2 tablets
36-47 | 4-5 years | 3 tablets
48-59 | 6-8 years | 4 tablets
60-71 | 9-10 years years | 5 tablets
72-95 | 11 | 6 tablets

Other information

- store at controlled room temperature 20-25ºC (68-77ºF). Avoid high humidity. Protect from light
- see end flap for expiration date and lot number

Inactive ingredients

citric acid, corn starch, crospovidone, D&C red 30 aluminum lake, dextrose, ethylcellulose, FD&C blue 1 aluminum lake, flavors, gelatin, maltodextrin, magnesium stearate, sucralose

Questions or comments?

1-866-467-2748

Product Packaging

NDC 68016-196-00

Compare to Children's Tylenol® Meltaways® Active Ingredient*

Premier Value

Children's
Pain Reliever

Ages 2-6

ACETAMINOPHEN

pain reliever/fever reducer
Aspirin Free/ Ibuprofen Free

GRAPE FLAVOR

30 count – 80mg each

TAMPER EVIDENT: DO NOT USE IF PRINTED SAFETY SEAL UNDER CAP IS BROKEN OR MISSING

*This product is not manufactured or distributed by McNeil Consumer Healthcare, owner of the registered trademark Children's Tylenol® Meltaways®.